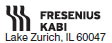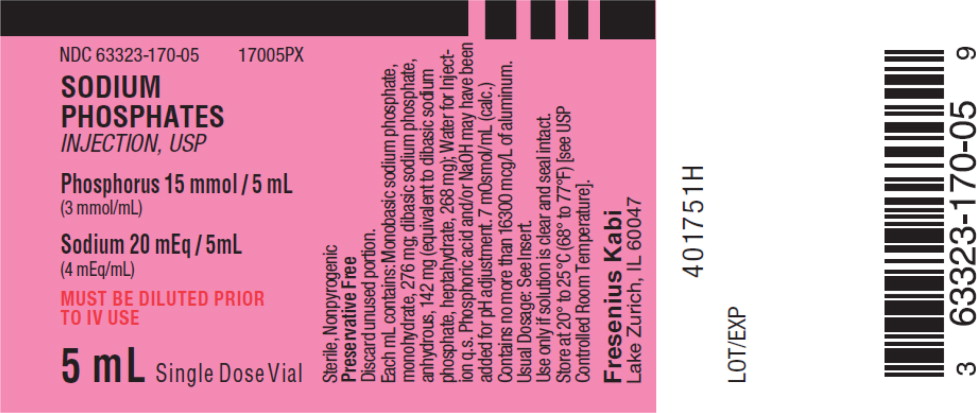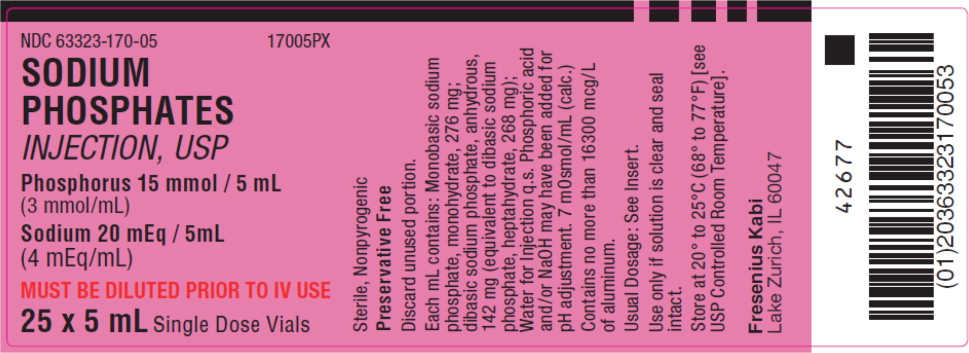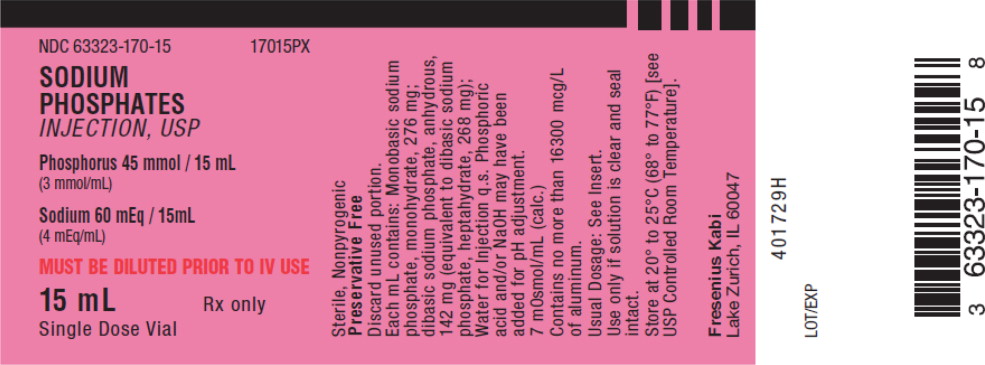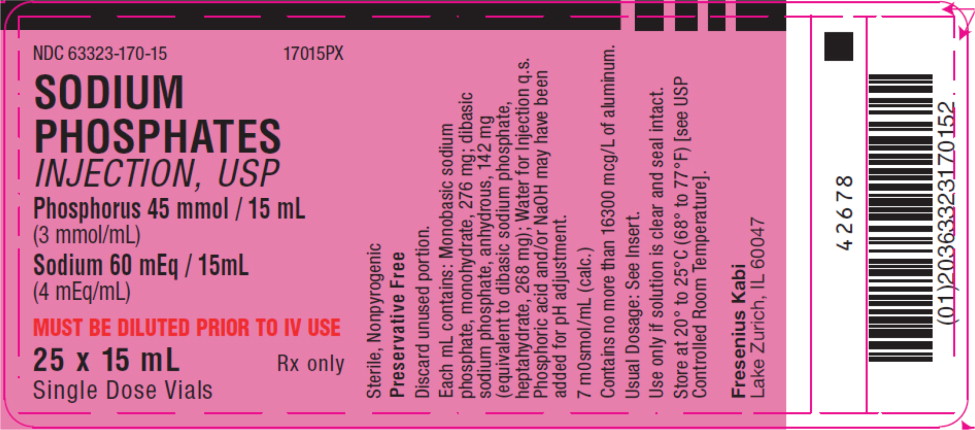 DRUG LABEL: Sodium Phosphates

NDC: 63323-170 | Form: INJECTION, SOLUTION
Manufacturer: Fresenius Kabi USA, LLC
Category: prescription | Type: HUMAN PRESCRIPTION DRUG LABEL
Date: 20210723

ACTIVE INGREDIENTS: SODIUM PHOSPHATE, MONOBASIC, MONOHYDRATE 276 mg/1 mL; SODIUM PHOSPHATE, DIBASIC, ANHYDROUS 142 mg/1 mL
INACTIVE INGREDIENTS: PHOSPHORIC ACID; SODIUM HYDROXIDE

Sodium Phosphates Injection USP

3 mmol P and 4 mEq Na^+/ mL

FOR ADDITIVE USE ONLY AFTER DILUTION IN IV FLUIDS

DESCRIPTION

Sodium Phosphates Injection, USP, 3 mmol/mL (millimoles/mL), is a sterile, nonpyrogenic, concentrated solution containing a mixture of monobasic sodium phosphate and dibasic sodium phosphate in Water for Injection.

The solution is administered after dilution by the intravenous route as an electrolyte replenisher. It must not be administered undiluted.

Each mL contains: Monobasic sodium phosphate, monohydrate, 276 mg; dibasic sodium phosphate, anhydrous, 142 mg (equivalent to dibasic sodium phosphate, heptahydrate, 268 mg); Water for Injection q.s. In the 5 mL and 15 mL product, phosphoric acid and/or NaOH may have been added for pH adjustment.

Each mL provides 3 mmol of phosphorus and 4 mEq sodium. It contains no bacteriostat, antimicrobial agent or added buffer. The pH is 5.7 (approx.). The osmolar concentration is 7 mOsmol/mL (calc.)

The solution is intended as an alternative to potassium phosphate to provide phosphate ion (PO4^3-) for addition to large volume infusion fluids for intravenous use.

Sodium Phosphates, USP, monohydrate monobasic is chemically designated NaH2PO4 • H2O. Occurs as white, odorless crystals or granules freely soluble in water.

Dibasic Sodium Phosphate, USP, anhydrous, is chemically designated Na2HPO4. Occurs as a colorless or white granular salt freely soluble in water.

CLINICAL PHARMACOLOGY

Phosphorus in the form of organic and inorganic phosphate has a variety of important biochemical functions in the body and is involved in many significant metabolic and enzyme reactions in almost all organs and tissues. It exerts a modifying influence on the steady state of calcium levels, a buffering effect on acid-base equilibrium and a primary role in the renal excretion of hydrogen ion.

Phosphorus is present in plasma and other extracellular fluid, in cell membranes and intracellular fluid, as well as in collagen and bone tissues. Phosphate in the extracellular fluid is primarily in inorganic form and plasma levels may vary somewhat with age. The ratio of disodium phosphate and monosodium phosphate in the extracellular fluid is 4 to 1 (80% to 20%) at the normal pH of 7.4. This buffer ratio varies with the pH, but owing to its relatively low concentration, it contributes little to the buffering capacity of the extracellular fluid.

Phosphate, present in large amounts in erythrocytes and other tissue cells, plays a significant intracellular role in the synthesis of high energy organic phosphates. It has been shown to be essential to maintain red cell glucose utilization, lactate production, and the concentration of both erythrocyte adenosine triphosphate (ATP) and 2,3 diphosphoglycerate (DPG), and must be deemed as important to other tissue cells. Hypophosphatemia should be avoided during periods of total parenteral nutrition (TPN), or other lengthy periods of intravenous infusions. It has been suggested that patients receiving TPN receive 20 mEq phosphate (13 mmol phosphate)/1000 kcal from dextrose. Serum phosphate levels should be regularly monitored and appropriate amounts of phosphate should be added to the infusions to maintain normal serum phosphate levels. Intravenous infusion of inorganic phosphate may be accompanied by a decrease in the serum level and urinary excretion of calcium. The normal level of serum inorganic phosphate is 3 to 4.5 mg/100 mL in adults; 4 to 7 mg/100 mL in children.

Intravenously infused phosphate not taken up by the tissues is excreted almost entirely in the urine. Plasma phosphate is believed to be filterable by the renal glomeruli, and the major portion of filtered phosphate (greater than 80%) is actively reabsorbed by the tubules. Many modifying influences tend to alter the amount excreted in the urine.

Sodium is the principal cation of extracellular fluid. It comprises more than 90% of the total cations at its normal plasma concentration of approximately 142 mEq/L. While the sodium ion can diffuse across cell membranes, intracellular sodium is maintained at a much lower concentration than extracellular sodium through the expenditure of energy by the cell (so-called ‘‘sodium cation pump’’). Loss of intracellular potassium ion is usually accompanied by an increase in intracellular sodium ion.

When serum sodium concentration is low, the secretion of antidiuretic hormone (ADH) by the pituitary is inhibited, thereby preventing water reabsorption by the distal renal tubules. On the other hand, adrenal secretion of aldosterone increases renal tubular reabsorption of sodium in an effort to re-establish normal serum sodium concentration.

INDICATIONS AND USAGE

Sodium Phosphates Injection, USP is indicated as a source of phosphate, for addition to large volume intravenous fluids, to prevent or correct hypophosphatemia in patients with restricted or no oral intake. It is also useful as an additive for preparing specific parenteral fluid formulas when the needs of the patient cannot be met by standard electrolyte or nutrient solutions.

The concomitant amount of sodium (4 mEq/mL) must be calculated into total electrolyte dose of such prepared solutions.

CONTRAINDICATIONS

Sodium phosphate is contraindicated in diseases where high phosphate or low calcium levels may be encountered, and in patients with hypernatremia.

WARNINGS

WARNING: This product contains aluminum that may be toxic. Aluminum may reach toxic levels with prolonged parenteral administration if kidney function is impaired. Premature neonates are particularly at risk because their kidneys are immature, and they require large amounts of calcium and phosphate solutions, which contain aluminum.

Research indicates that patients with impaired kidney function, including premature neonates, who receive parenteral levels of aluminum at greater than 4 to 5 mcg/kg/day accumulate aluminum at levels associated with central nervous system and bone toxicity. Tissue loading may occur at even lower rates of administration.

Sodium Phosphates Injection must be diluted and thoroughly mixed before use.

To avoid phosphate intoxication, infuse solutions containing sodium phosphate slowly. Infusing high concentrations of phosphate may result in a reduction of serum calcium and symptoms of hypocalcemic tetany. Calcium levels should be monitored.

Solutions containing sodium ion should be used with great care, if at all, in patients with congestive heart failure, severe renal insufficiency and in clinical states in which there exists edema with sodium retention.

In patients with diminished renal function, administration of solutions containing sodium ions may result in sodium retention.

PRECAUTIONS

General

Use with caution in patients with renal impairment, cirrhosis, cardiac failure or in conjunction with other edematous medications. It should not be used with sodium-retaining medications.

Caution must be exercised in the administration of parenteral fluids especially those containing sodium ion, to patients receiving corticosteroids or corticotropin.

Laboratory Tests

Phosphate replacement therapy with sodium phosphate should be guided primarily by serum inorganic phosphate levels and the limits imposed by the accompanying sodium (Na^+) ion. Frequent monitoring of serum calcium and sodium as well as renal function is recommended.

Drug Interactions

Concurrent use with thiazides may cause renal damage.

Pregnancy Category C

Animal reproduction studies have not been conducted with sodium phosphate. It is also not known whether sodium phosphate can cause fetal harm when administered to a pregnant woman or can affect reproduction capacity. Sodium phosphate should be given to a pregnant woman only if clearly needed.

Nursing Mothers

It is not known whether this drug is excreted in human milk. Because many drugs are excreted in human milk, caution should be exercised when sodium phosphate is administered to a nursing woman.

Geriatric Use

An evaluation of current literature revealed no clinical experience identifying differences in response between elderly and younger patients. In general, dose selection for an elderly patient should be cautious, usually starting at the low end of the dosing range, reflecting the greater frequency of decreased hepatic, renal, or cardiac function, and of concomitant disease or other drug therapy.

Sodium ions and phosphorus ions are known to be substantially excreted by the kidney, and the risk of toxic reactions may be greater in patients with impaired renal function. Because elderly patients are more likely to have decreased renal function, care should be taken in dose selection, and it may be useful to monitor renal function.

ADVERSE REACTIONS

Adverse reactions involve the possibility of phosphate intoxication. Phosphate intoxication results in a reduction of serum calcium and the symptoms are those of hypocalcemic tetany (see WARNINGS).

OVERDOSAGE

In the event of overdosage, discontinue infusions containing sodium phosphate immediately and institute corrective therapy to restore depressed serum calcium and to reduce elevated serum sodium levels. (see WARNINGS, PRECAUTIONS and ADVERSE REACTIONS)

DOSAGE AND ADMINISTRATION

Sodium Phosphates Injection is administered intravenously only after dilution and thorough mixing in a larger volume of fluid. The dose and rate of administration are dependent upon the individual needs of the patient. Serum sodium, inorganic phosphorus and calcium levels should be monitored as a guide to dosage. Using aseptic technique, all or part of the contents of one or more vials may be added to other intravenous fluids to provide any desired number of millimoles of phosphate and milliequivalents of sodium.

In patients on TPN, approximately 10 to 15 mmol of phosphorus (equivalent to 310 to 465 mg elemental phosphorus) per liter bottle of TPN solution is usually adequate to maintain normal serum phosphate, though larger amounts may be required in hypermetabolic states. The amount of sodium which accompanies the addition of phosphate also should be kept in mind, and if necessary, serum sodium levels should be monitored.

The suggested dose of phosphorus for infants receiving TPN is 1.5 to 2 mmol/kg/day.

Parenteral drug products should be inspected visually for particulate matter and discoloration prior to administration, whenever solution and container permit.

HOW SUPPLIED

Product No. | NDC No. | Volume
17005PX | 63323-170-05 | 5 mL in a 10 mL vial
17015PX | 63323-170-15 | 15 mL in a 30 mL vial
11850 | 63323-118-50 | 50 mL in a 50 mL vial

These vials are flip-top, Single Dose Vials, packaged 25 vials per tray. The vials marked with ‘‘PX’’ are partially filled to facilitate transfer of the contents.

Do not administer unless solution is clear and seal intact. Discard unused portion.

Store at 20° to 25°C (68° to 77°F) [see USP Controlled Room Temperature].

45780G

Revised: August 2017

PACKAGE LABEL – PRINCIPAL DISPLAY PANEL – Sodium Phosphates 5 mL Single Dose Vial Label

NDC 63323-170-05 17005PX

SODIUM PHOSPHATES

INJECTION, USP

Phosphorus 15 mmol / 5 mL

(3 mmol/mL)

Sodium 20 mEq / 5mL

(4 mEq/mL)

MUST BE DILUTED PRIOR TO IV USE

5 mL Single Dose Vial

PACKAGE LABEL – PRINCIPAL DISPLAY PANEL – Sodium Phosphates 5 mL Single Dose Vial Tray Label

NDC 63323-170-05 17005PX

SODIUM PHOSPHATES

INJECTION, USP

Phosphorus 15 mmol / 5 mL

(3 mmol/mL)

Sodium 20 mEq / 5mL

(4 mEq/mL)

MUST BE DILUTED PRIOR TO IV USE

25 x 5 mL Single Dose Vials

PACKAGE LABEL – PRINCIPAL DISPLAY PANEL – Sodium Phosphates 15 mL Single Dose Vial Label

NDC 63323-170-15 17015PX

SODIUM PHOSPHATES

INJECTION, USP

Phosphorus 45 mmol / 15 mL

(3 mmol/mL)

Sodium 60 mEq / 15mL

(4 mEq/mL)

MUST BE DILUTED PRIOR TO IV USE

15 mL Rx only

Single Dose Vial

PACKAGE LABEL – PRINCIPAL DISPLAY PANEL – Sodium Phosphates 15 mL Single Dose Vial Tray Label

NDC 63323-170-15 17015PX

SODIUM PHOSPHATES

INJECTION, USP

Phosphorus 45 mmol / 15 mL

(3 mmol/mL)

Sodium 60 mEq / 15mL

(4 mEq/mL)

MUST BE DILUTED PRIOR TO IV USE

25 x 15 mL Rx only

Single Dose Vials